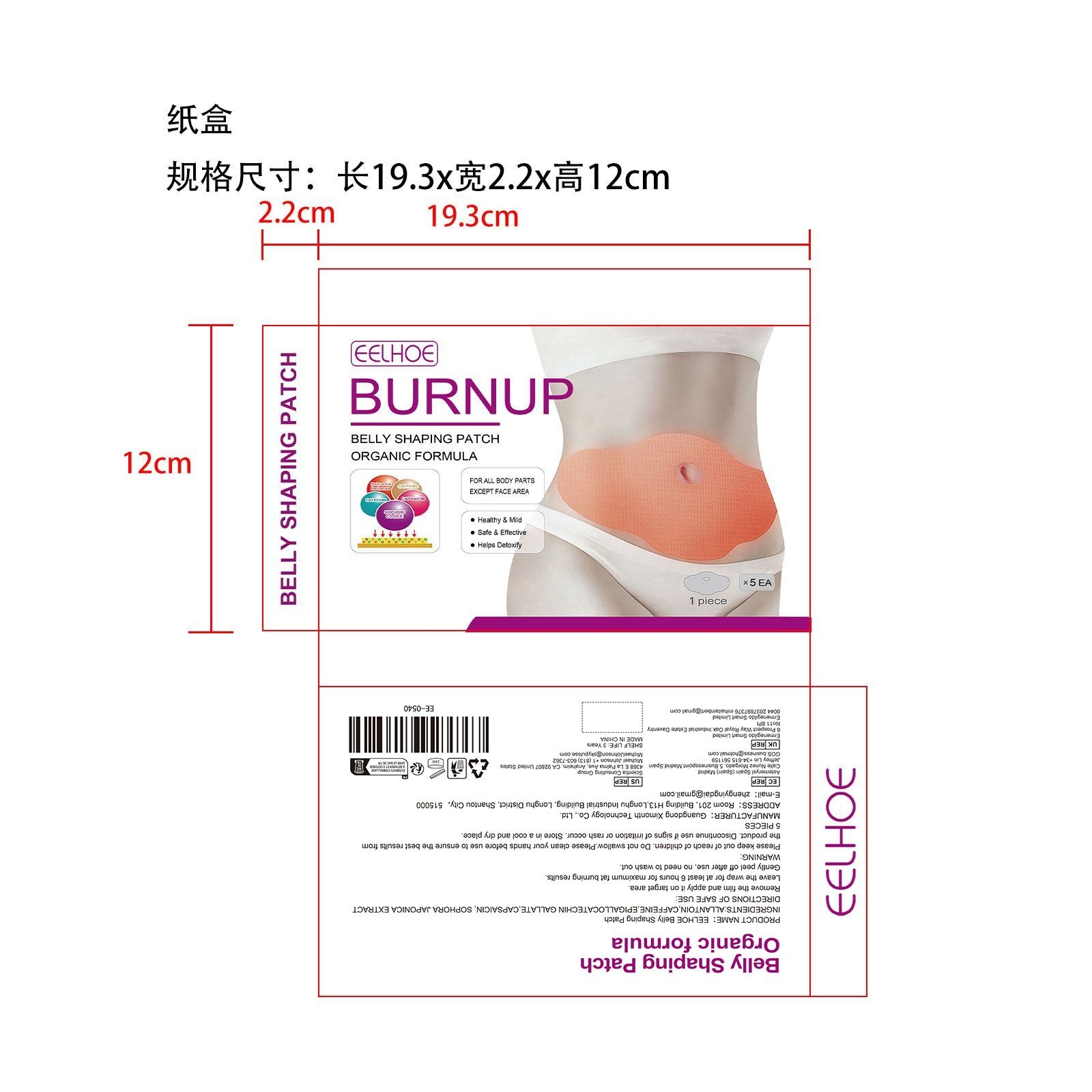 DRUG LABEL: Belly Shaping Patch
NDC: 84660-016 | Form: PATCH
Manufacturer: Guangdong Ximonth Technology Co., Ltd.
Category: otc | Type: HUMAN OTC DRUG LABEL
Date: 20240920

ACTIVE INGREDIENTS: CAFFEINE 13.25 g/53 g; EPIGALLOCATECHIN GALLATE 10.6 g/53 g; CAPSAICIN 7.95 g/53 g; STYPHNOLOBIUM JAPONICUM WHOLE 5.3 g/53 g
INACTIVE INGREDIENTS: ALLANTOIN 15.9 g/53 g

Active Ingredient(s)

CAFFEINE、EPIGALLOCATECHIN GALLATE、CAPSAICIN、SOPHORA JAPONICA EXTRACT

Purpose

Get in shape

Use

Remove the film and apply it on target area.Leave the wrap for at least 6 hours for maximum fat burning results.Gently peel off after use, no need to wash out.

Warnings

Please keep out of reach of children.Do not swallow.Please clean your hands before use to ensure the best results from the product.Discontinue use if signs of irritation or rash occur.Store in a cool and dry place.

Do not use

Discontinue use if signs of irritation or rash occur.

STOP USE

Discontinue use if signs of irritation or rash occur.

KEEP OUT OF REACH OF CHILDREN

Please keep out of reach of children. Do not swallow.

STORAGE AND HANDLING

Avoid freezing and excessive heat above 40C (104F) ）

Store in a cool and dry place.

INACTIVE INGREDIENT

ALLANTOIN